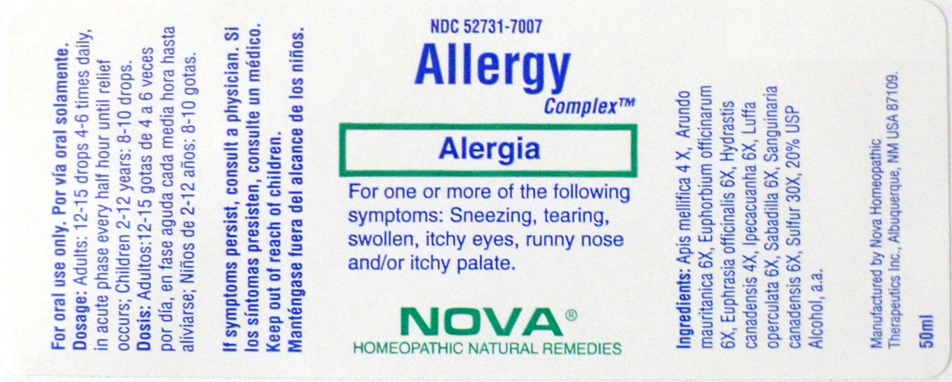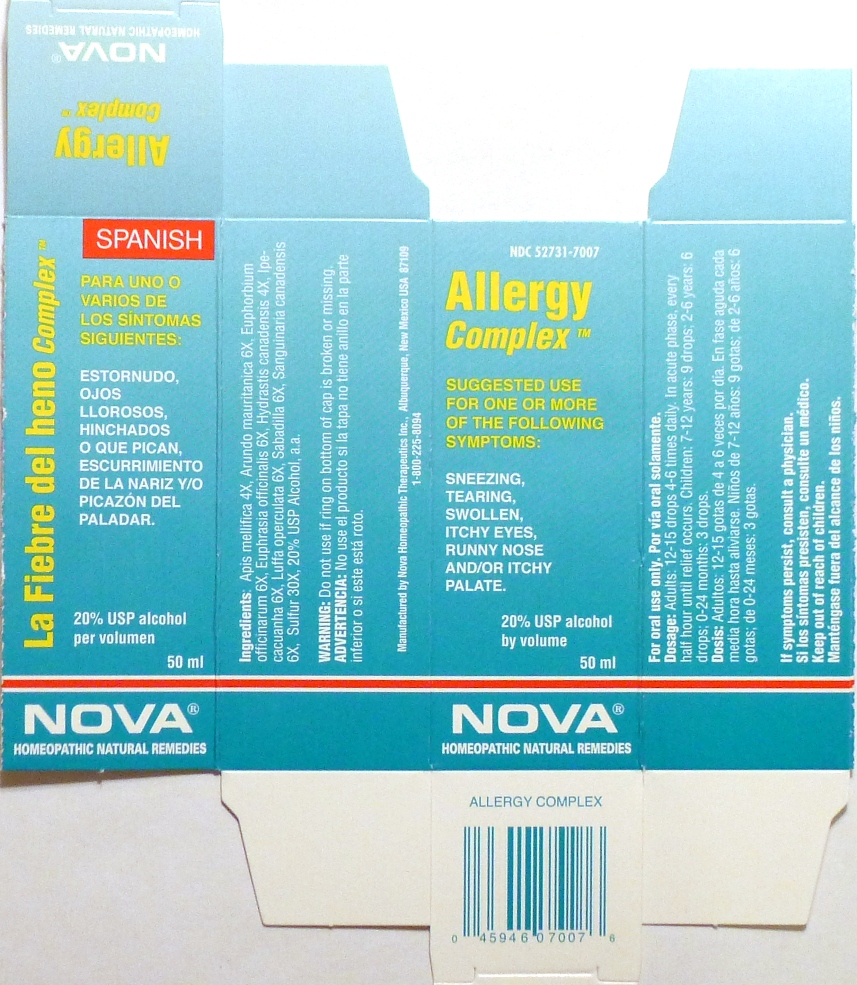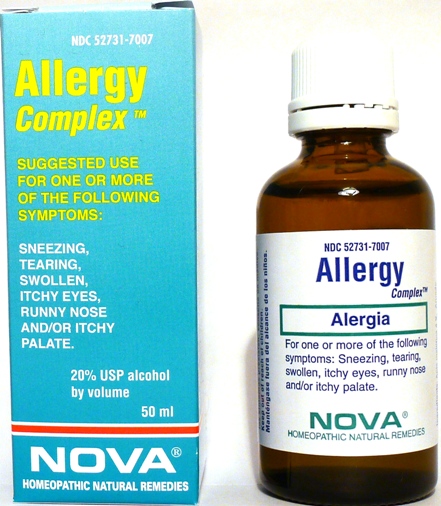 DRUG LABEL: Allergy Complex
NDC: 52731-7007 | Form: LIQUID
Manufacturer: Nova Homeopathic Therapeutics, Inc.
Category: homeopathic | Type: HUMAN OTC DRUG LABEL
Date: 20110601

ACTIVE INGREDIENTS: APIS MELLIFERA 4 [hp_X]/1 mL; ARUNDO PLINIANA ROOT 6 [hp_X]/1 mL; EUPHORBIA RESINIFERA RESIN 6 [hp_X]/1 mL; EUPHRASIA STRICTA 6 [hp_X]/1 mL; GOLDENSEAL 4 [hp_X]/1 mL; IPECAC 6 [hp_X]/1 mL; LUFFA OPERCULATA FRUIT 6 [hp_X]/1 mL; SCHOENOCAULON OFFICINALE SEED 6 [hp_X]/1 mL; SANGUINARIA CANADENSIS ROOT 6 [hp_X]/1 mL; SULFUR 30 [hp_X]/1 mL
INACTIVE INGREDIENTS: ALCOHOL

Allergy Complex

Purpose:

Suggested use for one or more of the following symptoms:

Sneezing, tearing, swollen, itchy eyes, runny nose and/or itchy palate.

Usage and Dosage:

For oral use only.

DOSAGE AND ADMINISTRATION

Adults:
In Acute Phase:
12-15 drops, every half hour until relief occurs
When Relief Occurs:
12-15 drops, 4-6 times per day
Children 2-12 years:
8-10 drops, 4-6 times per day

Infants 0-24 months:
3 drops, 4-6 times per day

Warnings:

Keep out of reach of children.

WARNINGS

If symptoms persist, consult a physician.
Do not use if ring on bottom of cap is broken or missing.

Active Ingredients:

Apis mellifica 4X, Arundo mauritanica 6X, Euphorbium officinarum 6X, Euphrasia officinalis 6X, Hydrastis canadensis 4X, Ipecacuanha 6X, Luffa operculata 6X, Sabadilla 6X, Sanguinaria canadensis 6X, Sulfur 30X

Inactive Ingredients:

Alcohol, 20% USP

QUESTIONS

Manufactured by Nova Homeopathic Therapeutics Inc., Albuquerque, New Mexico USA 87109
1-800-225-8094

PACKAGE LABEL

Allergy Complex Product

Allergy Complex Bottle Label

Allergy Complex Box